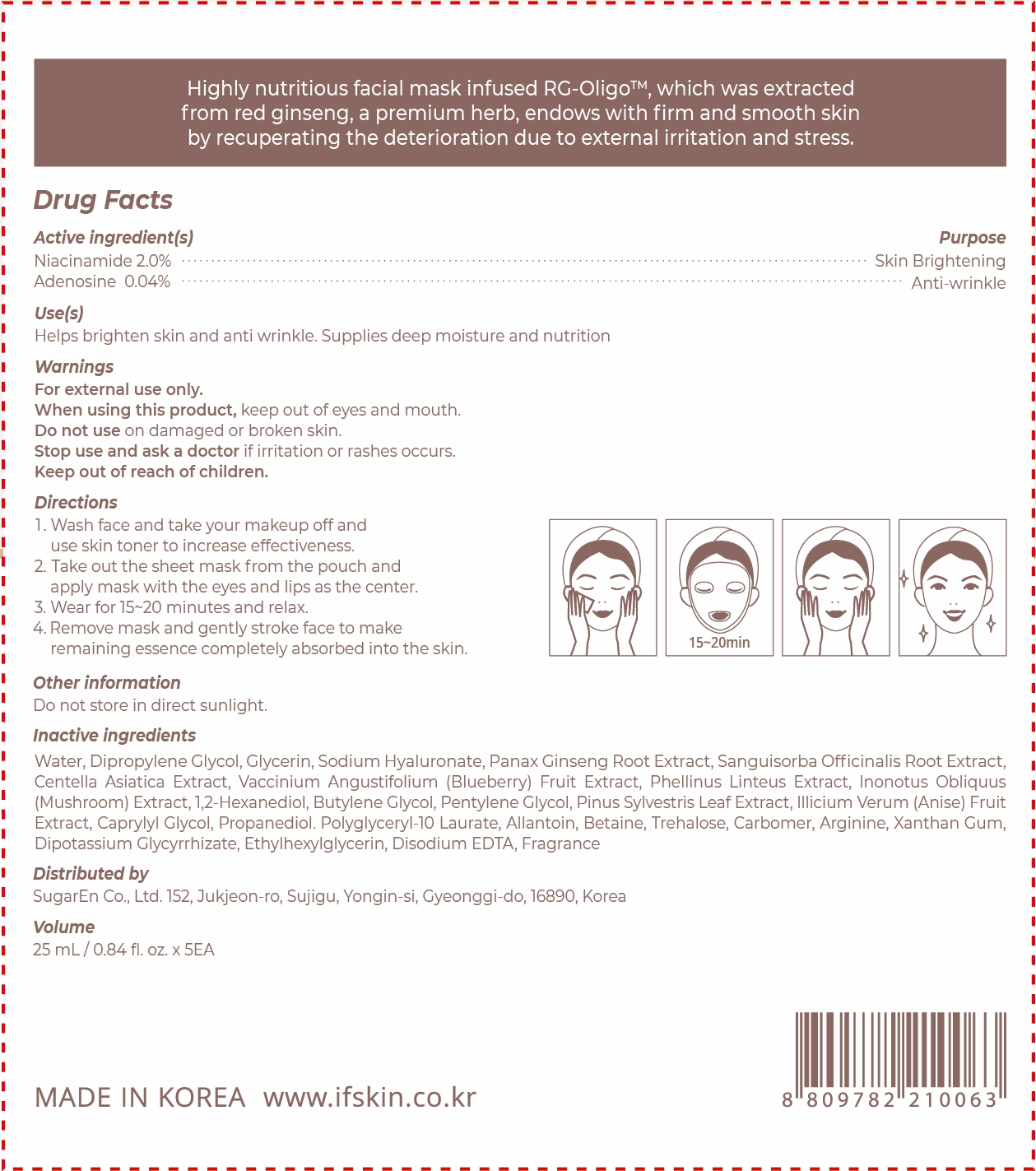 DRUG LABEL: RGO NUTRIMENT RICH MASK
NDC: 81897-505 | Form: LIQUID
Manufacturer: SugarEn Co., Ltd.
Category: otc | Type: HUMAN OTC DRUG LABEL
Date: 20210714

ACTIVE INGREDIENTS: NIACINAMIDE 2 g/100 mL; ADENOSINE 0.04 g/100 mL
INACTIVE INGREDIENTS: STAR ANISE FRUIT; ETHYLHEXYLGLYCERIN; HYALURONATE SODIUM; 1,2-HEXANEDIOL; PENTYLENE GLYCOL; CAPRYLYL GLYCOL; BETAINE; TREHALOSE; ARGININE; XANTHAN GUM; GLYCYRRHIZINATE DIPOTASSIUM; LOWBUSH BLUEBERRY; WATER; GLYCERIN; ASIAN GINSENG; SANGUISORBA OFFICINALIS ROOT; PHELLINUS LINTEUS MYCELIUM; INONOTUS OBLIQUUS FRUITING BODY; BUTYLENE GLYCOL; PINE NEEDLE OIL (PINUS SYLVESTRIS); PROPANEDIOL; POLYGLYCERYL-10 LAURATE; ALLANTOIN; CARBOMER HOMOPOLYMER, UNSPECIFIED TYPE; DIPROPYLENE GLYCOL; CENTELLA ASIATICA; EDETATE DISODIUM ANHYDROUS

81897-505 RGO NUTRIMENT RICH MASK

Active ingredient(s)

Niacinamide 2.0%

Adenosine 0.04%

Purpose

Skin Brightening, Anti-wrinkle

Use(s)

Helps brighten skin and anti wrinkle.

Supplies deep moisture and nutrition

Warnings

For external only.

When using this product,

keep out of eyes and mouth.

Do not use

on damaged or broken skin.

Stop use and ask a doctor

if irritation or rashes occurs.

Keep out of reach of children.

Other information

Do not store in direct sunlight.

Directions

1. Wash face and take your makeup off and use skin toner to increase effectiveness.

2. Take out the sheet mask from the pouch and apply mask with the eyes and lips as the center.

3. Wear for 15~20 minutes and relax.

4. Remove mask and gently stroke face to make remaining essence completely absorbed into the skin.

Inactive indredients

Water, Dipropylene Glycol, Glycerin, Sodium Hyaluronate, Panax Ginseng Root Extract, Sanguisorba Officinalis Root Extract, Centella Asiatica Extract, Vaccinium Angustifolium (Blueberry) Fruit Extract, Phellinus Linteus Extract, lnonotus Obliquus (Mushroom) Extract, 1,2-Hexanediol, Butylene Glycol, Pentylene Glycol, Pinus Sylvestris Leaf Extract, lllicium Verum (Anise) Fruit Extract, Caprylyl Glycol, Propanediol. Polyglyceryl-10 Laurate, Allantoin, Betaine, Trehalose, Carbomer, Arginine, Xanthan Gum, Dipotassium Glycyrrhizate, Ethylhexylglycerin, Disodium EDTA, Fragrance